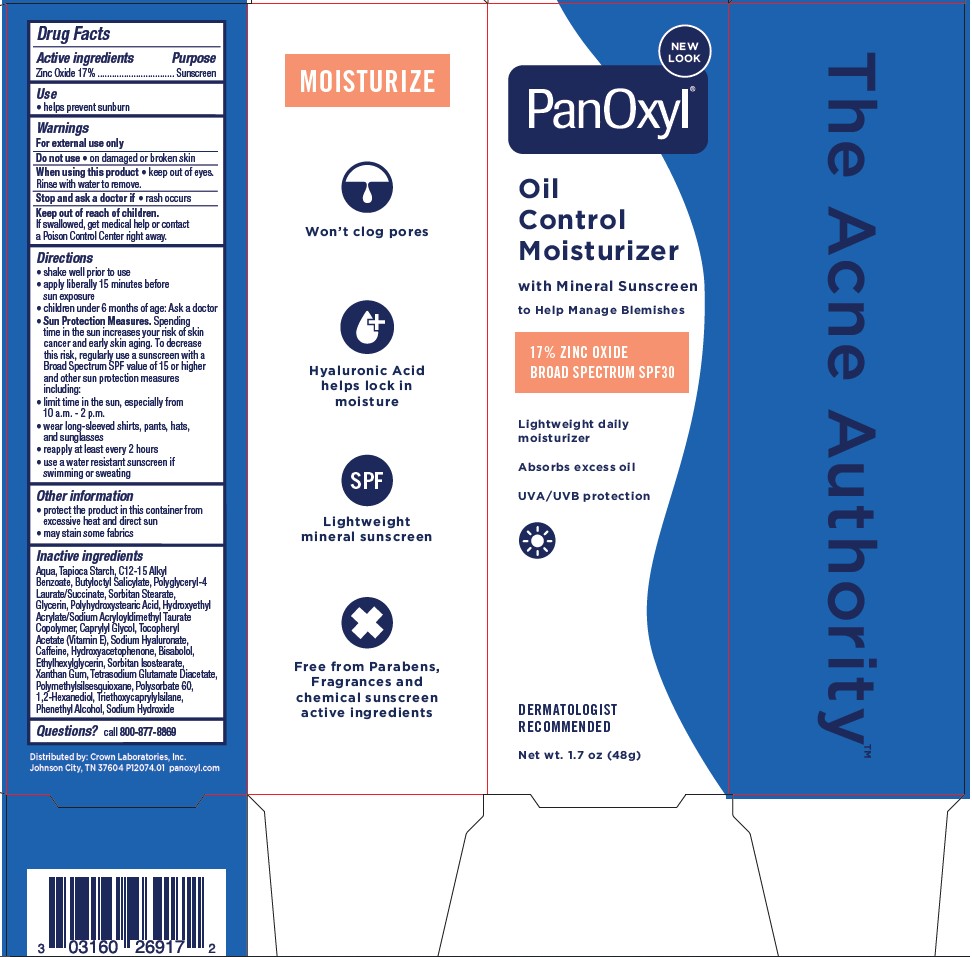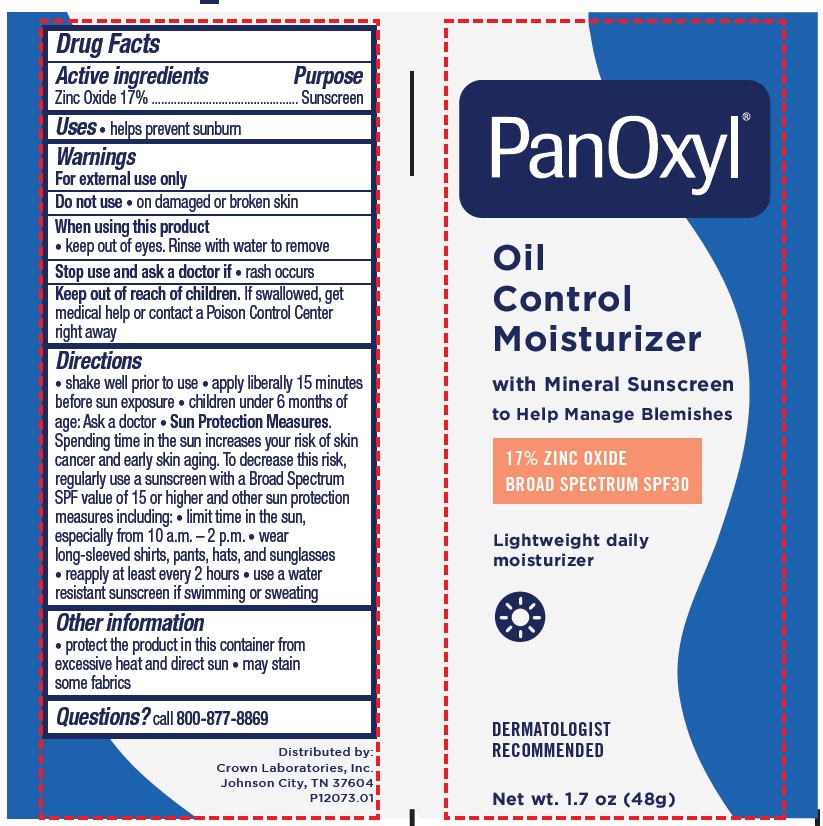 DRUG LABEL: PanOxyl Oil AM Control Moisturizer
NDC: 0316-0269 | Form: LOTION
Manufacturer: Crown Laboratories
Category: otc | Type: HUMAN OTC DRUG LABEL
Date: 20260112

ACTIVE INGREDIENTS: ZINC OXIDE 170 mg/1 g
INACTIVE INGREDIENTS: LEVOMENOL; BUTYLOCTYL SALICYLATE; ALKYL (C12-15) BENZOATE; CAFFEINE; CAPRYLYL GLYCOL; ETHYLHEXYLGLYCERIN; GLYCERIN; 1,2-HEXANEDIOL; HYDROXYACETOPHENONE; HYDROXYETHYL ACRYLATE/SODIUM ACRYLOYLDIMETHYL TAURATE COPOLYMER (45000 MPA.S AT 1%); PHENYLETHYL ALCOHOL; POLYGLYCERYL-4 LAURATE/SUCCINATE; SORBITAN MONOSTEARATE; STARCH, TAPIOCA; POLYHYDROXYSTEARIC ACID (2300 MW); POLYMETHYLSILSESQUIOXANE (11 MICRONS); POLYSORBATE 60; WATER; .ALPHA.-TOCOPHEROL ACETATE; TRIETHOXYCAPRYLYLSILANE; XANTHAN GUM; SODIUM HYDROXIDE; SORBITAN ISOSTEARATE; TETRASODIUM GLUTAMATE DIACETATE; HYALURONATE SODIUM

PanOxyl Oil Control Moisturizer with SPF 30 Mineral Sunscreen

Active Ingredients

Zinc Oxide 17%

Purpose

Sunscreen

Use

- helps prevent sunburn

Warnings

For external use only

Do not use

- on damaged or broken skin

When using this product

- keep out of eyes. Rinse with water to remove.

Stop and ask a doctor if

- rash occurs

Keep out of reach of children.

If swallowed, get medical help or contact a Poison Control Center right away.

Directions

• shake well prior to use

• apply liberally 15 minutes before sun exposure

• children under 6 months of age: Ask a doctor

• Sun Protection Measures: Spending time in the sun increases your risk of skin cancer and early skin aging. To decrease this risk, regularly use a sunscreen with a Broad Spectrum SPF value of 15 or higher and other sun protection measures including:

• limit time in the sun, especially from 10 a.m. - 2 p.m.

• wear long-sleeved shirts, pants, hats, and sunglasses.

• reapply at least every 2 hours

• use a water resistant suscreen if swimming for sweating

Other Information

- protect the product in this container from excessive heat and direct sun
- may stain some fabrics

Inactive Ingredients

Bisabolol, Butyloctyl Salicylate, C12-15 Alkyl Benzoate, Caffeine, Caprylyl Glycol, Ethylhexylglycerin, Glycerin, 1,2-Hexanediol, Hydroxyacetophenone, Hydroxyethyl Acrylate/Sodium Acryloyldimethyl Taurate Copolymer, Phenethyl Alcohol, Polyglyceryl-4 Laurate/Succinate, Polyhydroxystearic Acid, Polymethylsilsesquioxane, Polysorbate 60, Purified Water, Sodium Hyaluronate, Sodium Hydroxide, Sorbitan Isostearate, Sorbitan Monostearate, Tapioca Starch, Tetrasodium Glutamate Diacetate, Tocopheryl Acetate (Vitamin E),Triethoxycaprylylsilane, Xanthan Gum

Questions?

Call 1-800-877-8869

RECENT MAJOR CHANGES

Update title of section.

Formatted Uses section

Formatted Directions section

Updated Uses section

Updated Directions to follow monograph

PanOxyl Oil Control Moisturizer 1.7oz Tube

DERMATOLOGIST RECOMMENDED

PanOxyl AM

OIL CONTROL MOISTURIZER

Broad Spectrum SPF 30

Mineral Sunscreen

Lightweight Daily Moisturizer

Absorbs Excess Oil

UVA/UVB Protection

Won't Clog Pores

Net wt. 1.7oz (48g)

P12073.01

PanOxyl Oil Control Moisturizer 1.7oz Carton

PanOxyl

Oil Control Moisturizer

with Mineral Sunscreen

to Help Manage Blemishes

17% ZINC OXIDE

BROAD SPECTRUM SPF 30

Lightweight daily moisturizer

Absorbs excess oil

UVA/UVB Protection

DERMATOLOGIST RECOMMENDED

Net wt. 1.7 oz (48 g)

P12074.01